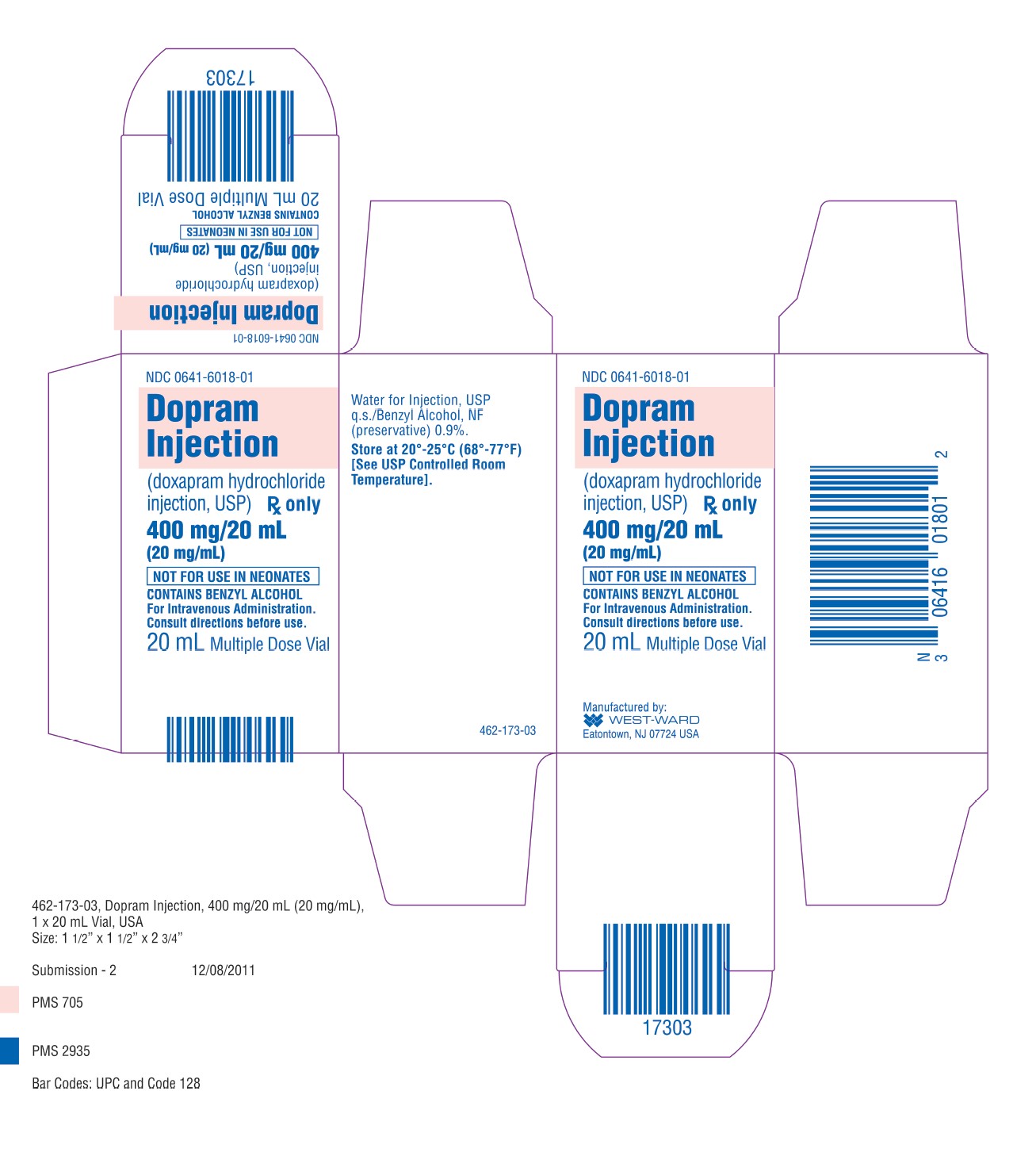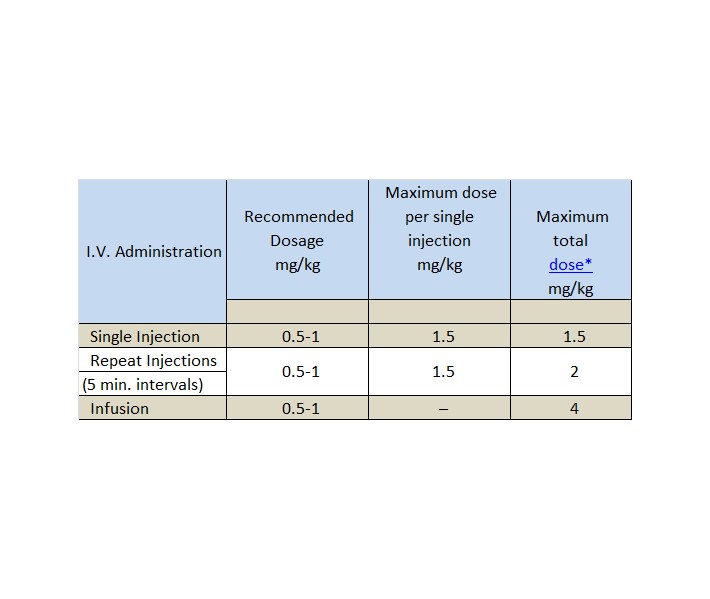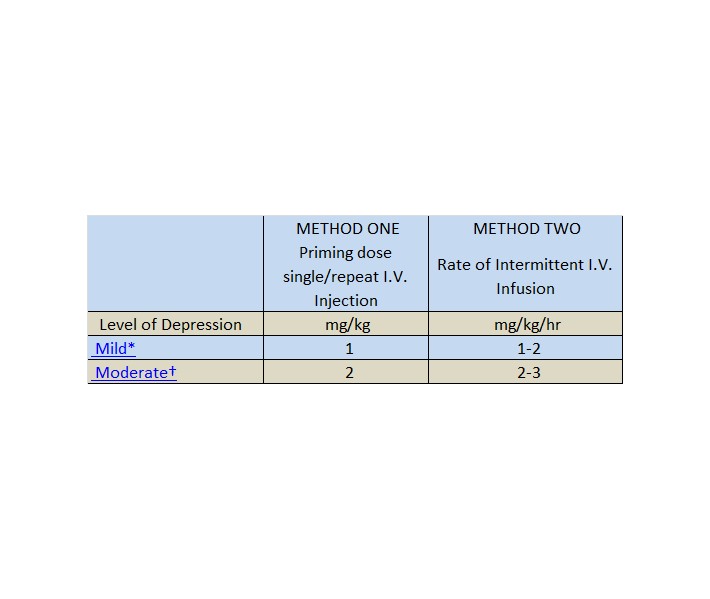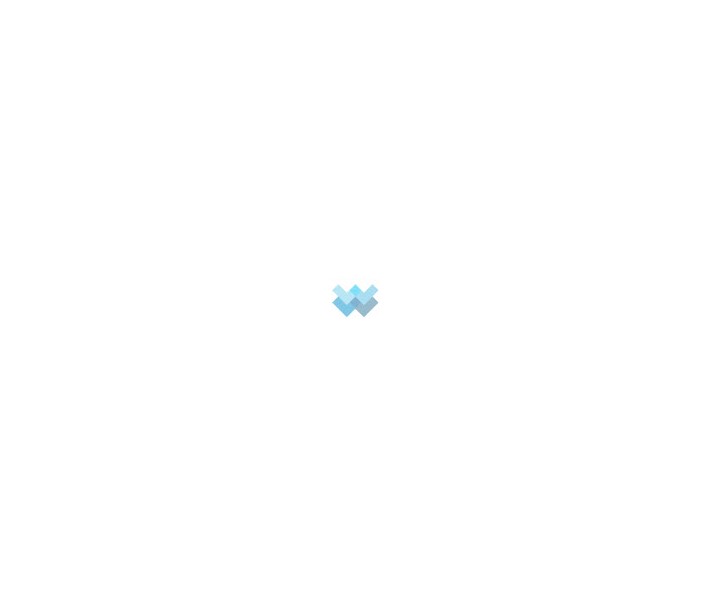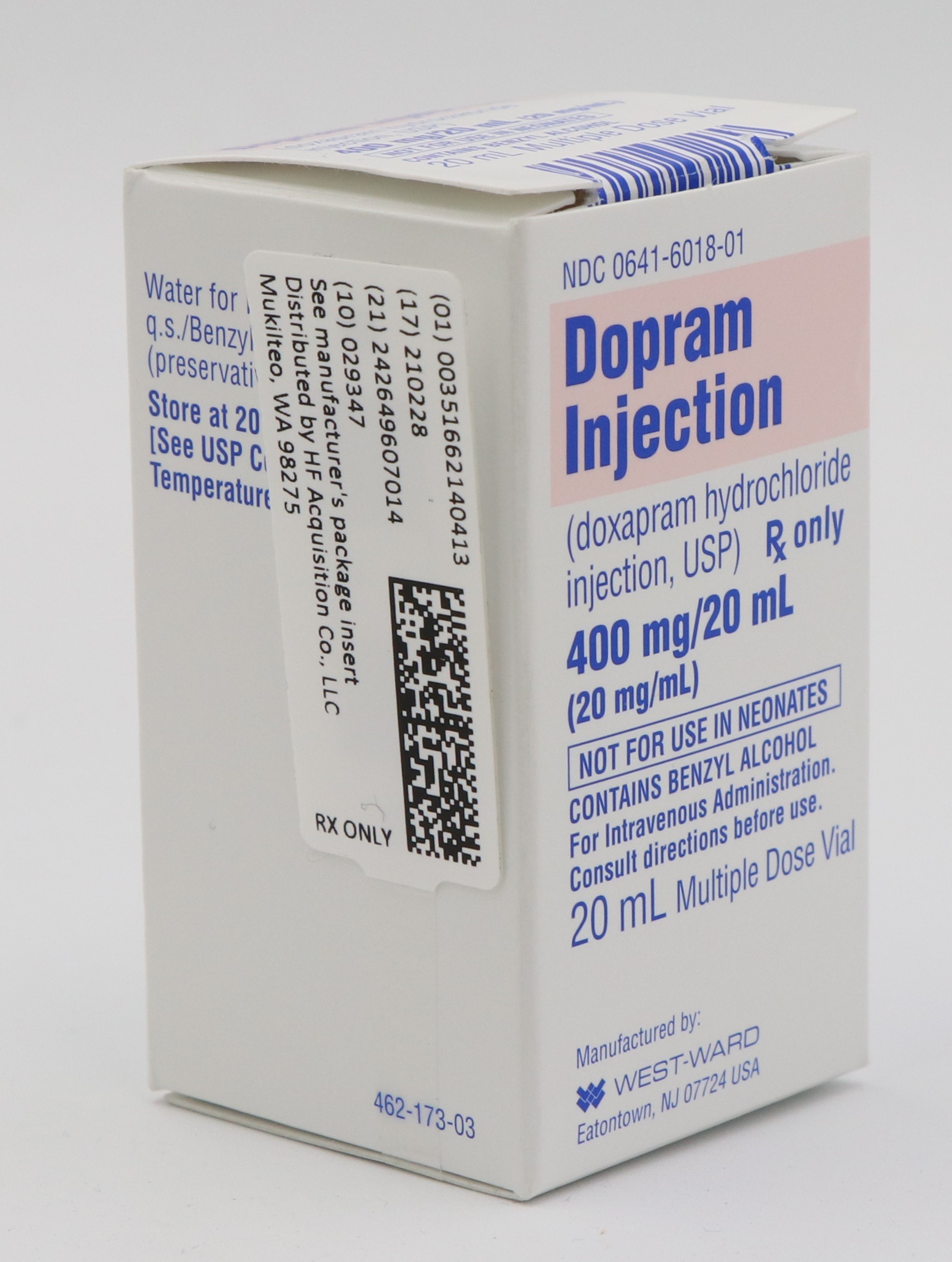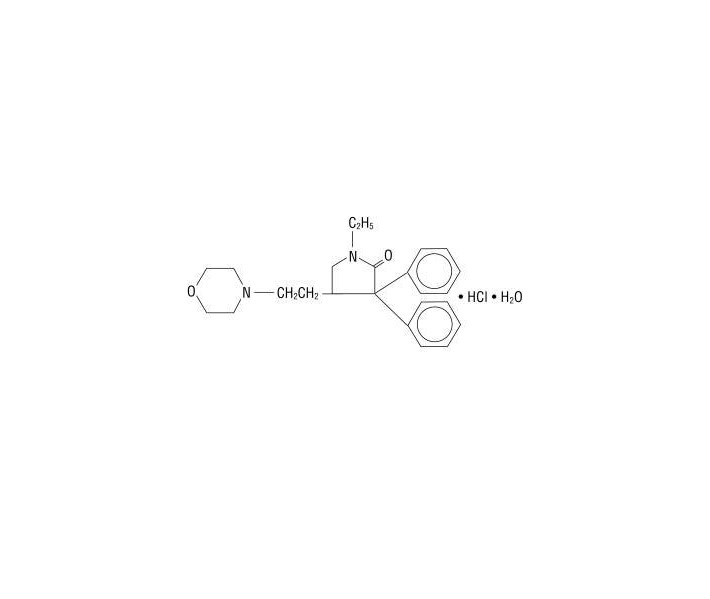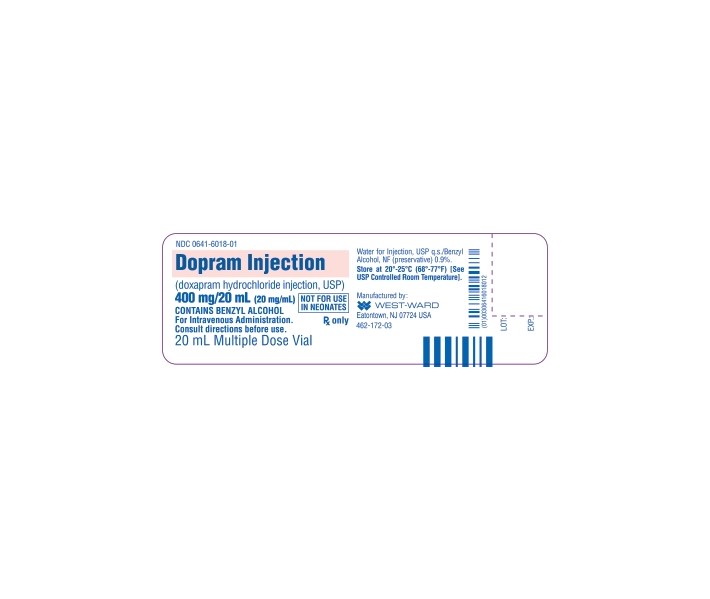 DRUG LABEL: DOXAPRAM HYDROCHLORIDE
NDC: 51662-1404 | Form: INJECTION
Manufacturer: HF Acquisition Co LLC, DBA HealthFirst
Category: prescription | Type: HUMAN PRESCRIPTION DRUG LABEL
Date: 20250108

ACTIVE INGREDIENTS: DOXAPRAM HYDROCHLORIDE 20 mg/1 mL
INACTIVE INGREDIENTS: BENZYL ALCOHOL 9 mg/1 mL; WATER

DOPRAM INJECTION (DOXAPRAM HYDROCHLORIDE INJECTION, USP) 400 mg/20 mL (20 mg/mL) 20 mL VIAL BOXED

SPL UNCLASSIFIED

NOT FOR USE IN NEONATES
CONTAINS BENZYL ALCOHOL
Rx only

DESCRIPTION

DOPRAM Injection (doxapram hydrochloride injection, USP) is a clear, colorless, sterile, non-pyrogenic, aqueous solution with pH 3.5 to 5, for intravenous administration.

Each 1 mL contains:

Doxapram Hydrochloride, USP ................................................................. 20 mg
Benzyl Alcohol, NF (as preservative) ......................................................... 0.9%
Water for Injection, USP ...........…................................................................. q.s.

Doxapram Injection is a respiratory stimulant.

Doxapram hydrochloride is a white to off-white, crystalline powder, sparingly soluble in water, alcohol and chloroform. Chemically, doxapram hydrochloride is 1-ethyl-4-[2-(4-morpholinyl)ethyl]-3,3-diphenyl-2-pyrrolidinone monohydrochloride, monohydrate.

The chemical structure is:

C24H31ClN2O2 • H2O M.W. 432.98

CLINICAL PHARMACOLOGY

Pharmacodynamics

Doxapram hydrochloride produces respiratory stimulation mediated through the peripheral carotid chemoreceptors. As the dosage level is increased, the central respiratory centers in the medulla are stimulated with progressive stimulation of other parts of the brain and spinal cord.

The onset of respiratory stimulation following the recommended single intravenous injection of doxapram hydrochloride usually occurs in 20 to 40 seconds with peak effect at 1 to 2 minutes. The duration of effect may vary from 5 to 12 minutes.

The respiratory stimulant action is manifested by an increase in tidal volume associated with a slight increase in respiratory rate.

A pressor response may result following doxapram administration. Provided there is no impairment of cardiac function, the pressor effect is more marked in hypovolemic than in normovolemic states. The pressor response is due to the improved cardiac output rather than peripheral vasoconstriction. Following doxapram administration, an increased release of catecholamines has been noted.

Although opiate-induced respiratory depression is antagonized by doxapram, the analgesic effect is not affected.

Pharmacokinetics

Doxapram is metabolized via ring hydroxylation to ketodoxapram, an active metabolite readily detected in the plasma.

INDICATIONS & USAGE

Postanesthesia

When the possibility of airway obstruction and/or hypoxia have been eliminated, doxapram may be used to stimulate respiration in patients with drug-induced postanesthesia respiratory depression or apnea other than that due to muscle relaxant drugs.
To pharmacologically stimulate deep breathing in the postoperative patient. (A quantitative method of assessing oxygenation, such as pulse oximetry, is recommended.)

Drug-Induced Central Nervous System Depression

Exercising care to prevent vomiting and aspiration, doxapram may be used to stimulate respiration, hasten arousal, and to encourage the return of laryngopharyngeal reflexes in patients with mild to moderate respiratory and CNS depression due to drug overdosage.

Chronic Pulmonary Disease Associated with Acute Hypercapnia

Doxapram is indicated as a temporary measure in hospitalized patients with acute respiratory insufficiency superimposed on chronic obstructive pulmonary disease. Its use should be for a short period of time (see DOSAGE & ADMINISTRATION) as an aid in the prevention of elevation of arterial CO2 tension during the administration of oxygen.

It should not be used in conjunction with mechanical ventilation.

CONTRAINDICATIONS

Doxapram is contraindicated in patients with known hypersensitivity to the drug or any of the injection components.

Doxapram should not be used in patients with epilepsy or other convulsive disorders.

Doxapram is contraindicated in patients with proven or suspected pulmonary embolism.

Doxapram is contraindicated in patients with mechanical disorders of ventilation such as mechanical obstruction, muscle paresis (including neuromuscular blockade), flail chest, pneumothorax, acute bronchial asthma, pulmonary fibrosis, or other conditions resulting in restriction of the chest wall, muscles of respiration, or alveolar expansion.

Doxapram is contraindicated in patients with evidence of head injury, cerebral vascular accident, or cerebral edema, and in those with significant cardiovascular impairment, uncompensated heart failure, severe coronary artery disease, or severe hypertension, including that associated with hyperthyroidism or pheochromocytoma. (See WARNINGS.)

WARNINGS

Doxapram should not be used in conjunction with mechanical ventilation.

Exposure to excessive amounts of benzyl alcohol has been associated with toxicity (hypotension, metabolic acidosis), particularly in neonates, and an increased incidence of kernicterus, particularly in small preterm infants. There have been rare reports of deaths, primarily in preterm infants, associated with exposure to excessive amounts of benzyl alcohol. The amount of benzyl alcohol from medications is usually considered negligible compared to that received in flush solutions containing benzyl alcohol. Administration of high dosages of medications containing this preservative must take into account the total amount of benzyl alcohol administered. The amount of benzyl alcohol at which toxicity may occur is not known. If the patient requires more than the recommended dosages or other medications containing this preservative, the practitioner must consider the daily metabolic load of benzyl alcohol from these combined sources (see PRECAUTIONS, Pediatric Use).

In Postanesthetic Use

Doxapram is neither an antagonist to muscle relaxant drugs nor a specific narcotic antagonist. More specific tests (eg, peripheral nerve stimulation, airway pressures, head lift, pulse oximetry, and end-tidal carbon dioxide) to assess adequacy of ventilation are recommended before administering doxapram.
Doxapram should be administered with great care and only under careful supervision to patients with hypermetabolic states such as hyperthyroidism or pheochromocytoma.
Since narcosis may recur after stimulation with doxapram, care should be taken to maintain close observation until the patient has been fully alert for ½ to 1 hour.
In patients who have received general anesthesia utilizing a volatile agent known to sensitize the myocardium to catecholamines, administration of doxapram should be delayed until the volatile agent has been excreted in order to lessen the potential for arrhythmias, including ventricular tachycardia and ventricular fibrillation (see PRECAUTIONS, Drug Interactions).

In Drug-Induced CNS and Respiratory Depression

Doxapram alone may not stimulate adequate spontaneous breathing or provide sufficient arousal in patients who are severely depressed either due to respiratory failure or to CNS depressant drugs, but may be used as an adjunct to established supportive measures and resuscitative techniques.

In Chronic Obstructive Pulmonary Disease

Because of the associated increased work of breathing, do not increase the rate of infusion of doxapram in severely ill patients in an attempt to lower pCO2.

PRECAUTIONS

General

An adequate airway is essential and airway protection should be considered since doxapram may stimulate vomiting.
Recommended dosages of doxapram should be employed and maximum total dosages should not be exceeded. In order to avoid side effects, it is advisable to use the minimum effective dosage.
Monitoring of the blood pressure, pulse rate, and deep tendon reflexes is recommended to prevent overdosage.
Vascular extravasation or use of a single injection site over an extended period should be avoided since either may lead to thrombophlebitis or local skin irritation.
Rapid infusion may result in hemolysis.
Lowered pCO2 induced by hyperventilation produces cerebral vasoconstriction and slowing of the cerebral circulation. This should be taken into consideration on an individual basis. In certain patients a pressor effect of doxapram on the pulmonary circulation may result in a fall of the arterial pO2 probably due to a worsening of ventilation perfusion-matching in the lungs despite an overall improvement in alveolar ventilation and a fall in pCO2. Patients should be carefully supervised taking into account available blood gas measurements.
There is a risk that doxapram will produce adverse effects (including seizures) due to general central nervous system stimulation. Muscle involvement may range from fasciculation to spasticity. Anticonvulsants such as intravenous short-acting barbiturates, along with oxygen and resuscitative equipment should be readily available to manage overdosage manifested by excessive central nervous system stimulation. Slow administration of the drug and careful observation of the patient during administration and for some time subsequently are advisable. These precautions are to assure that the protective reflexes have been restored and to prevent possible post-hyperventilation or hypoventilation.
Doxapram should be administered cautiously to patients receiving sympathomimetic or monoamine oxidase inhibiting drugs, since an additive pressor effect may occur.
Blood pressure increases are generally modest but significant increases have been noted in some patients. Because of this, doxapram is not recommended for use in patients with severe hypertension (see CONTRAINDICATIONS).
Cardiovascular effects may include various dysrhythmias. Patients receiving doxapram should be monitored for disturbance of their cardiac rhythm.
If sudden hypotension or dyspnea develops, doxapram should be stopped.
Doxapram should be administered with caution to patients with significantly impaired hepatic or renal function as a reduction in the rate of metabolism or excretion of metabolites may alter the response.

In Postanesthetic Use

The same consideration to pre-existing disease states should be exercised as in non-anesthetized individuals. See CONTRAINDICATIONS and WARNINGS covering use in hypertension, asthma, disturbances of respiratory mechanics including airway obstruction, CNS disorders including increased cerebrospinal fluid pressure, convulsive disorders, acute agitation, and profound metabolic disorders.
See PRECAUTIONS, Drug Interactions.

In Chronic Obstructive Pulmonary Disease

Arrhythmias seen in some patients in acute respiratory failure secondary to chronic obstructive pulmonary disease are probably the result of hypoxia. Doxapram should be used with caution in these patients.
Arterial blood gases should be drawn prior to the initiation of doxapram infusion and oxygen administration, then at least every ½ hour during the infusion period to prevent development of CO2 retention and acidosis in patients with chronic obstructive pulmonary disease with acute hypercapnia. Doxapram administration does not diminish the need for careful monitoring of the patient or the need for supplemental oxygen in patients with acute respiratory failure. Doxapram should be stopped if the arterial blood gases deteriorate, and mechanical ventilation should be initiated.

Drug Interactions

Administration of doxapram to patients who are receiving sympathomimetic or monoamine oxidase inhibiting drugs may result in an additive pressor effect (see PRECAUTIONS, General).

In patients who have received neuromuscular blocking agents, doxapram may temporarily mask the residual effects of these drugs.

In patients who have received general anesthesia utilizing a volatile agent known to sensitize the myocardium to catecholamines, administration of doxapram should be delayed until the volatile agent has been excreted in order to lessen the potential for arrhythmias, including ventricular tachycardia and ventricular fibrillation (see WARNINGS).

There may be an interaction between doxapram and aminophylline and between doxapram and theophylline manifested by increased skeletal muscle activity, agitation, and hyperactivity.

Carcinogenesis, Mutagenesis, Impairment of Fertility

No carcinogenic or mutagenic studies have been performed using doxapram. Doxapram did not adversely affect the breeding performance of rats.

Pregnancy

PREGNANCY CATEGORY B

Reproduction studies have been performed in rats at doses up to 1.6 times the human dose and have revealed no evidence of impaired fertility or harm to the fetus due to doxapram. There are, however, no adequate and well-controlled studies in pregnant women. Because the animals in the reproduction studies were dosed by the IM and oral routes and animal reproduction studies, in general, are not always predictive of human response, this drug should be used during pregnancy only if clearly needed.

Nursing Mothers

It is not known whether this drug is excreted in human milk. Because many drugs are excreted in human milk, caution should be exercised when doxapram hydrochloride is administered to a nursing woman.

Pediatric Use

Safety and effectiveness in pediatric patients below the age of 12 years have not been established. This product contains benzyl alcohol as a preservative. Benzyl alcohol, a component of this product, has been associated with serious adverse events and death, particularly in pediatric patients. The “gasping syndrome”, (characterized by central nervous system depression, metabolic acidosis, gasping respirations, and high levels of benzyl alcohol and its metabolites found in the blood and urine) has been associated with benzyl alcohol dosages >99 mg/kg/day in neonates and low-birth-weight neonates. Additional symptoms may include gradual neurological deterioration, seizures, intracranial hemorrhage, hematologic abnormalities, skin breakdown, hepatic and renal failure, hypotension, bradycardia, and cardiovascular collapse. Although normal therapeutic doses of this product deliver amounts of benzyl alcohol that are substantially lower than those reported in association with the “gasping syndrome”, the minimum amount of benzyl alcohol at which toxicity may occur is not known. Premature and low-birth-weight infants, as well as patients receiving high dosages, may be more likely to develop toxicity. Practitioners administering this and other medications containing benzyl alcohol should consider the combined daily metabolic load of benzyl alcohol from all sources.

Premature neonates given doxapram have developed hypertension, irritability, jitteriness, hyperglycemia, glucosuria, abdominal distension, increased gastric residuals, vomiting, bloody stools, necrotizing enterocolitis, erratic limb movements, excessive crying, disturbed sleep, premature eruption of teeth, and QT prolongation that has resulted in heart block. In premature neonates with risk factors such as a previous seizure, perinatal asphyxia, or intracerebral hemorrhage, seizures have occurred. In many instances, doxapram was administered following administration of xanthine derivatives such as caffeine, aminophylline or theophylline.

ADVERSE REACTIONS

Adverse reactions reported coincident with the administration of DOPRAM (doxapram hydrochloride, USP) include:

1. Central and Autonomic Nervous Systems

Pyrexia, flushing, sweating; pruritus and paresthesia, such as a feeling of warmth, burning, or hot sensation, especially in the area of genitalia and perineum; apprehension, disorientation, pupillary dilatation, hallucinations, headache, dizziness, hyperactivity, involuntary movements, muscle spasticity, muscle fasciculations, increased deep tendon reflexes, clonus, bilateral Babinski, and convulsions.

2. Respiratory

Dyspnea, cough, hyperventilation, tachypnea, laryngospasm, bronchospasm, hiccough, and rebound hypoventilation.

3. Cardiovascular

Phlebitis, variations in heart rate, lowered T-waves, arrhythmias (including ventricular tachycardia and ventricular fibrillation), chest pain, tightness in chest. A mild to moderate increase in blood pressure is commonly noted and may be of concern in patients with severe cardiovascular diseases.

4. Gastrointestinal

Nausea, vomiting, diarrhea, desire to defecate.

5. Genitourinary

Stimulation of urinary bladder with spontaneous voiding; urinary retention. Elevation of BUN and albuminuria.

6. Hemic and Lymphatic

Hemolysis with rapid infusion. A decrease in hemoglobin, hematocrit, or red blood cell count has been observed in postoperative patients. In the presence of pre-existing leukopenia, a further decrease in WBC has been observed following anesthesia and treatment with doxapram hydrochloride.

OVERDOSAGE

Signs and Symptoms

Symptoms of overdosage are extensions of the pharmacologic effects of the drug. Excessive pressor effect, such as hypertension, tachycardia, skeletal muscle hyperactivity, and enhanced deep tendon reflexes may be early signs of overdosage. Therefore, the blood pressure, pulse rate, and deep tendon reflexes should be evaluated periodically and the dosage or infusion rate adjusted accordingly.

Other effects may include agitation, confusion, sweating, cough, and dyspnea.

Convulsive seizures are unlikely at recommended dosages. In unanesthetized animals, the convulsant dose is 70 times greater than the respiratory stimulant dose. Intravenous LD50 values in the mouse and rat were approximately 75 mg/kg and in the cat and dog were 40 to 80 mg/kg.

Except for management of chronic obstructive pulmonary disease associated with acute hypercapnia, the maximum recommended dosage is 3 GRAMS/24 HOURS. (See DOSAGE & ADMINISTRATION.)

Management

There is no specific antidote for doxapram. Management should be symptomatic. Anticonvulsants, along with oxygen and resuscitative equipment should be readily available to manage overdosage manifested by excessive central nervous system stimulation. Slow administration of the drug and careful observation of the patient during administration and for some time subsequently are advisable. These precautions are to assure that the protective reflexes have been restored and to prevent possible post-hyperventilation or hypoventilation.

There is no evidence that doxapram is dialyzable; further, the half-life of doxapram makes it unlikely that dialysis would be appropriate in managing overdose with this drug.

Close

DOSAGE & ADMINISTRATION

NOTE: CONTAINS BENZYL ALCOHOL (see PRECAUTIONS)

In Postanesthetic Use

Table I. Dosage for postanesthetic use-I.V. and infusion.

*
Dose not to exceed 3 grams/24 hours.

BY I.V. INJECTION

(See Table I. Dosage for postanesthetic use—I.V.)

The recommended dose for I.V. administration is 0.5 – 1 mg/kg for a single injection and at 5-minute intervals. Careful observation of the patient during administration and for some time subsequently are advisable. The maximum total dosage by I.V. injection is 2 mg/kg.

BY INFUSION

The solution is prepared by adding 250 mg of doxapram (12.5 mL) to 250 mL of dextrose 5% or 10% in water or normal saline solution. The infusion is initiated at a rate of approximately 5 mg/minute until a satisfactory respiratory response is observed, and maintained at a rate of 1 to 3 mg/minute. The rate of infusion should be adjusted to sustain the desired level of respiratory stimulation with a minimum of side effects. The maximum total dosage by infusion is 4 mg/kg, or approximately 300 mg for the average adult.

In the Management of Drug-Induced CNS Depression

(See Table II. Dosage for drug-induced CNS depression.)

Table II. Dosage for drug-induced CNS depression.

*
Mild Depression
Class 0: Asleep, but can be aroused and can answer questions.
Class 1: Comatose, will withdraw from painful stimuli, reflexes intact.
†
Moderate Depression
Class 2: Comatose, will not withdraw from painful stimuli, reflexes intact.
Class 3: Comatose, reflexes absent, no depression of circulation or respiration.

METHOD ONE

Using Single and/or Repeat Single I.V. Injections

Give priming dose of 2 mg/kg body weight and repeat in 5 minutes. The priming dose for moderate depression is 2 mg/kg and the priming dose for mild depression is 1 mg/kg.
Repeat same dose q 1 to 2h until patient wakens. Watch for relapse into unconsciousness or development of respiratory depression, since DOPRAM does not affect the metabolism of CNS-depressant drugs.
If relapse occurs, resume injections q 1 to 2h until arousal is sustained, or total maximum daily dose (3 grams) is given. After maximum dose has been given (3 grams), allow patient to sleep until 24 hours have elapsed from first injection of DOPRAM, using assisted or automatic respiration if necessary.
Repeat procedure the following day until patient breathes spontaneously and sustains desired level of consciousness, or until maximum dosage (3 grams) is given.
Repetitive doses should be administered only to patients who have shown response to the initial dose.
Failure to respond appropriately indicates the need for neurologic evaluation for a possible central nervous system source of sustained coma.

METHOD TWO

By Intermittent I.V. Infusion

Give priming dose as in Method One.
If patient wakens, watch for relapse; if no response, continue general supportive treatment for 1 to 2 hours and repeat priming dose of DOPRAM. If some respiratory stimulation occurs, prepare I.V. infusion by adding 250 mg of DOPRAM (12.5 mL) to 250 mL of saline or dextrose solution. Deliver at rate of 1 to 3 mg/min (60 to 180 mL/hr) according to size of patient and depth of coma. Discontinue DOPRAM if patient begins to waken or at end of 2 hours.
Continue supportive treatment for ½ to 2 hours and repeat Step b.
Do not exceed 3 grams/day.

Chronic Obstructive Pulmonary Disease Associated with Acute Hypercapnia

One vial of doxapram (400 mg) should be mixed with 180 mL of dextrose 5% or 10% or normal saline solution (concentration of 2 mg/mL). The infusion should be started at 1 to 2 mg/minute (½ to 1 mL/minute); if indicated, increase to a maximum of 3 mg/minute. Arterial blood gases should be determined prior to the onset of doxapram’s administration and at least every half hour during the two hours of infusion to insure against the insidious development of CO2-RETENTION AND ACIDOSIS. Alteration of oxygen concentration or flow rate may necessitate adjustment in the rate of doxapram infusion.
Predictable blood gas patterns are more readily established with a continuous infusion of doxapram. If the blood gases show evidence of deterioration, the infusion of doxapram should be discontinued.
ADDITIONAL INFUSIONS BEYOND THE SINGLE MAXIMUM TWO HOUR ADMINISTRATION PERIOD ARE NOT RECOMMENDED.

Parenteral drug products should be inspected visually for particulate matter and discoloration prior to administration, whenever solution and container permit.

Diluent Compatibility

Doxapram hydrochloride is compatible with 5% and 10% dextrose in water or normal saline.

Incompatibility

ADMIXTURE OF DOXAPRAM WITH ALKALINE SOLUTIONS SUCH AS 2.5% THIOPENTAL SODIUM, SODIUM BICARBONATE, FUROSEMIDE, OR AMINOPHYLLINE WILL RESULT IN PRECIPITATION OR GAS FORMATION.

Doxapram is also not compatible with ascorbic acid, cefoperazone sodium, cefotaxime sodium, cefotetan sodium, cefuroxime sodium, folic acid, dexamethasone disodium phosphate, diazepam, hydrocortisone sodium phosphate, methylprednisolone sodium, or hydrocortisone sodium succinate.

Admixture of doxapram and ticarcillin disodium results in an 18% loss of doxapram in 3 hours. When doxapram is mixed with minocycline hydrochloride, there is a loss of 8% of doxapram in 3 hours and a 13% loss of doxapram in 6 hours.

HOW SUPPLIED

DOPRAM INJECTION (DOXAPRAM HYDROCHLORIDE INJECTION, USP) is supplied in the following dosage forms.
NDC 51662-1404-1
DOPRAM INJECTION (DOXAPRAM HYDROCHLORIDE INJECTION, USP) 400 mg/20 mL (20 mg/mL) 20 mL VIAL BOXED

HF Acquisition Co LLC, DBA HealthFirst
Mukilteo, WA 98275

Also supplied in the following manufacture supplied dosage forms

DOPRAM Injection (doxapram hydrochloride injection, USP) is available in boxes of six 20 mL multiple dose vials containing 20 mg of doxapram hydrochloride per mL with benzyl alcohol 0.9% as the preservative (NDC 0641-6018-06).

Store at Controlled Room Temperature, Between 20˚C to 25˚C (68˚F to 77˚F). See USP.

SPL UNCLASSIFIED

To report SUSPECTED ADVERSE REACTIONS, contact West-Ward Pharmaceutical Corp. at 1-877-845-0689, or the FDA at 1-800-FDA-1088 or www.fda.gov/medwatch.

For Product Inquiry call 1-877-845-0689.

Manufactured by:

WEST-WARD
PHARMACEUTICALS
Eatontown, NJ 07724 USA

Revised November 2011

462-175-06